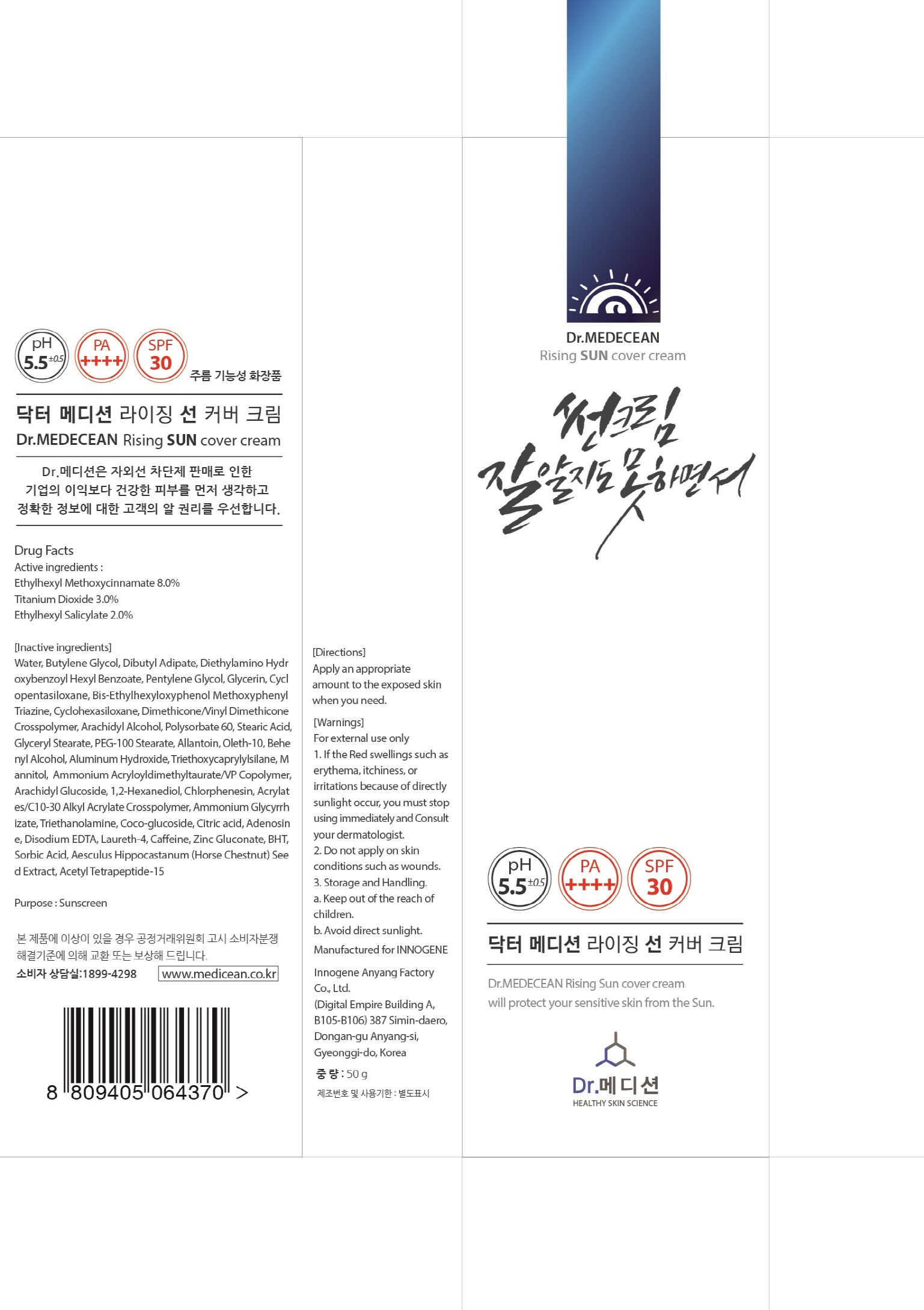 DRUG LABEL: Dr MEDECEAN Rising Sun Cover
NDC: 70540-040 | Form: CREAM
Manufacturer: INNOGENE CO.,LTD
Category: otc | Type: HUMAN OTC DRUG LABEL
Date: 20170927

ACTIVE INGREDIENTS: Octinoxate 4.0 g/50 g; Titanium Dioxide 1.5 g/50 g; Octisalate 1.0 g/50 g
INACTIVE INGREDIENTS: WATER; BUTYLENE GLYCOL

ACTIVE INGREDIENT

Active ingredients: Ethylhexyl Methoxycinnamate 8.0%, Titanium Dioxide 3.0%, Ethylhexyl Salicylate 2.0%

INACTIVE INGREDIENT

Inactive ingredients: Water, Butylene Glycol, Dibutyl Adipate, Diethylamino Hydroxybenzoyl Hexyl Benzoate, Pentylene Glycol, Glycerin, Cyclopentasiloxane, Bis-Ethylhexyloxyphenol Methoxyphenyl Triazine, Cyclohexasiloxane, Dimethicone/Vinyl Dimethicone Crosspolymer, Arachidyl Alcohol, Polysorbate 60, Stearic Acid, Glyceryl Stearate, PEG-100 Stearate, Allantoin, Oleth-10, Behenyl Alcohol, Aluminum Hydroxide, Triethoxycaprylylsilane, Mannitol, Ammonium Acryloyldimethyltaurate/VP Copolymer, Arachidyl Glucoside, 1,2-Hexanediol, Chlorphenesin, Acrylates/C10-30 Alkyl Acrylate Crosspolymer, Ammonium Glycyrrhizate, Triethanolamine, Coco-glucoside, Citric acid, Adenosine, Disodium EDTA, Laureth-4, Caffeine, Zinc Gluconate, BHT, Sorbic Acid, Aesculus Hippocastanum (Horse Chestnut) Seed Extract, Acetyl Tetrapeptide-15

PURPOSE

Purpose: Sunscreen

WARNINGS

Warnings: For external use only

1. If the Red swellings such as erythema, itchiness, or irritations because of directly sunlight occur, you must stop using immediately and Consult your dermatologist. 2. Do not apply on skin conditions such as wounds. 3. Storage and Handling. a. Keep out of the reach of children. b. Avoid direct sunlight.

DESCRIPTION

Uses: Dr.MEDECEAN Rising Sun Cover Cream will protect your sensitive skin from the Sun.

Directions: Apply an appropriate amount to the exposed skin when you need.